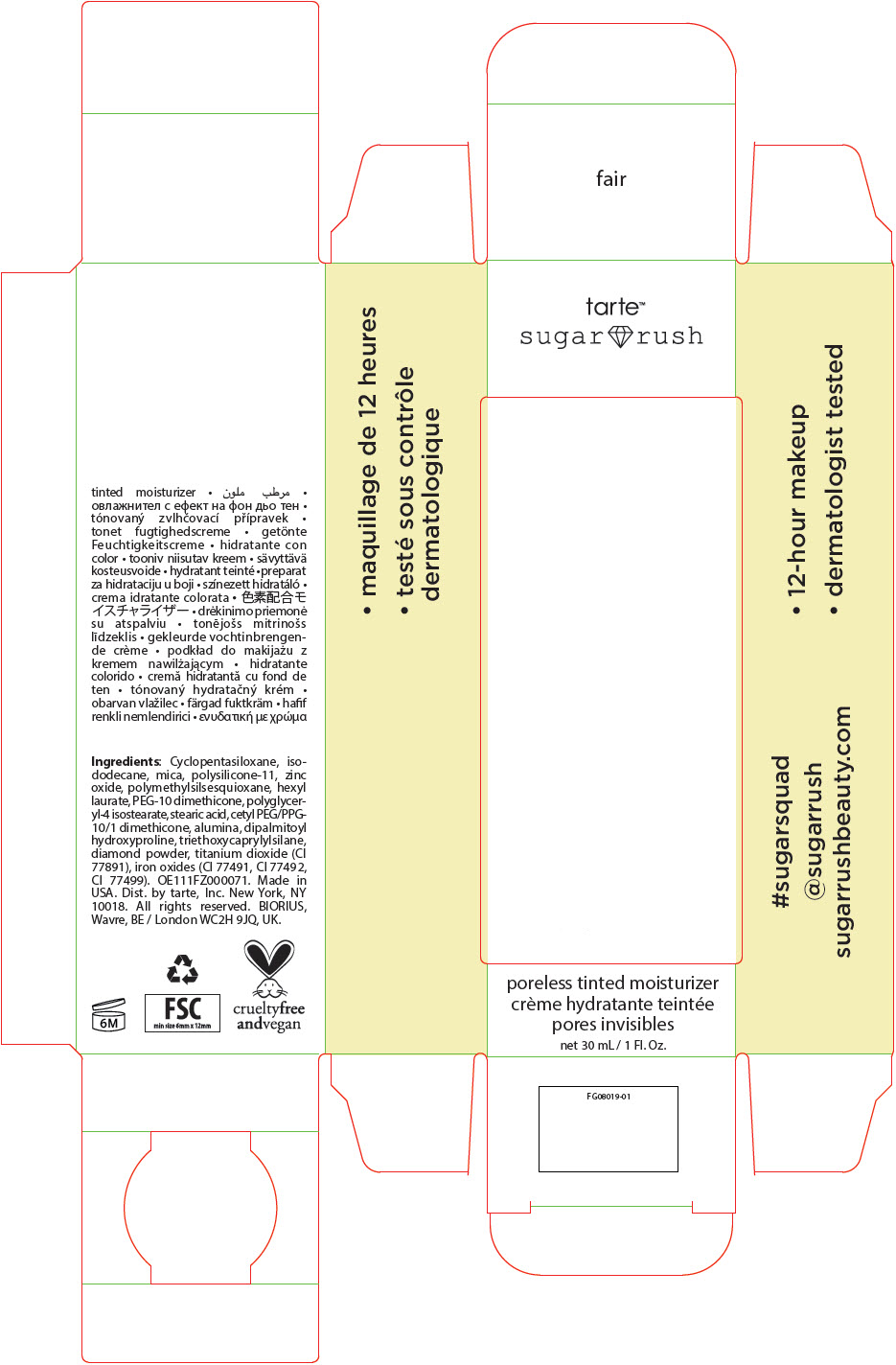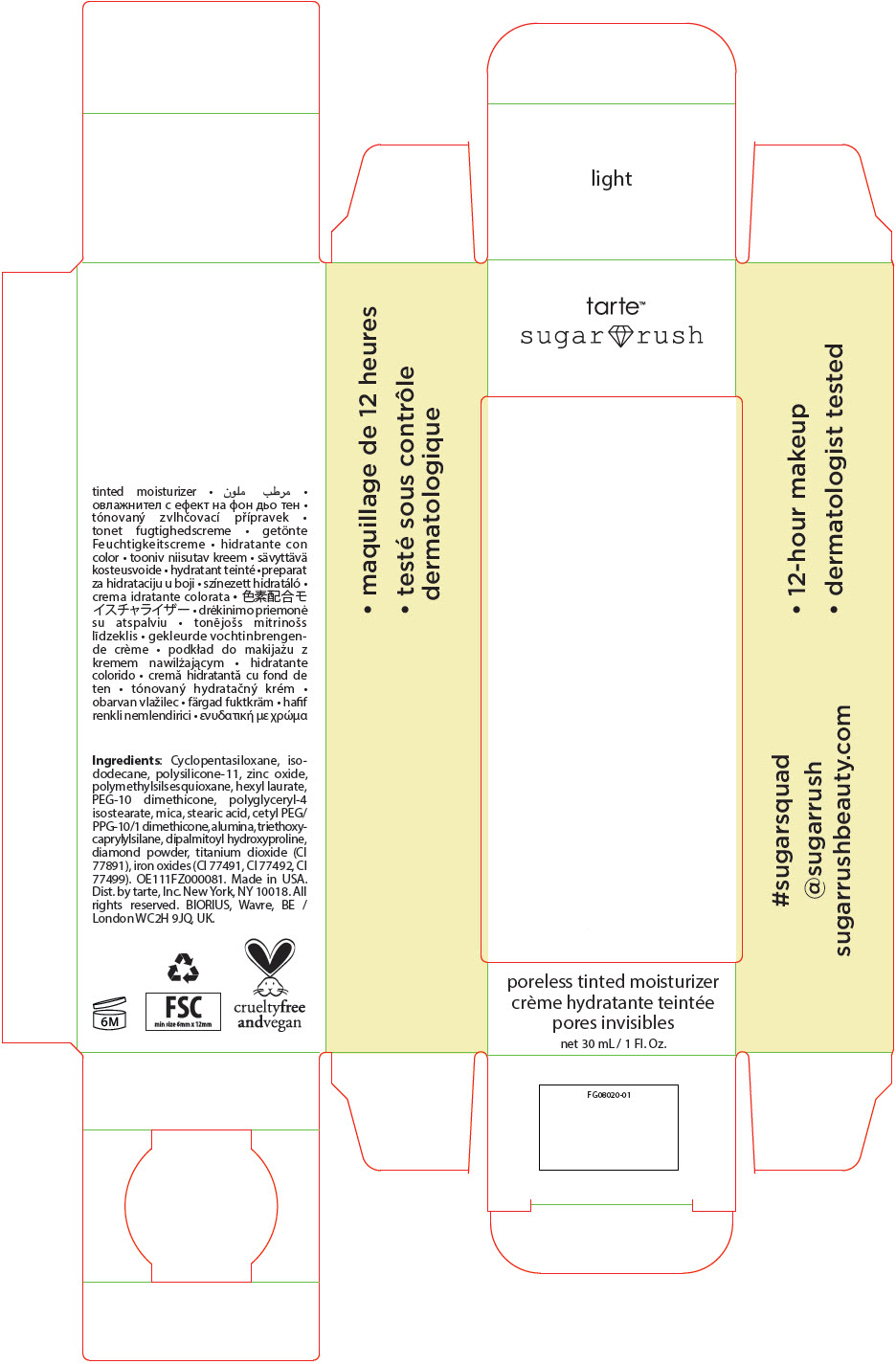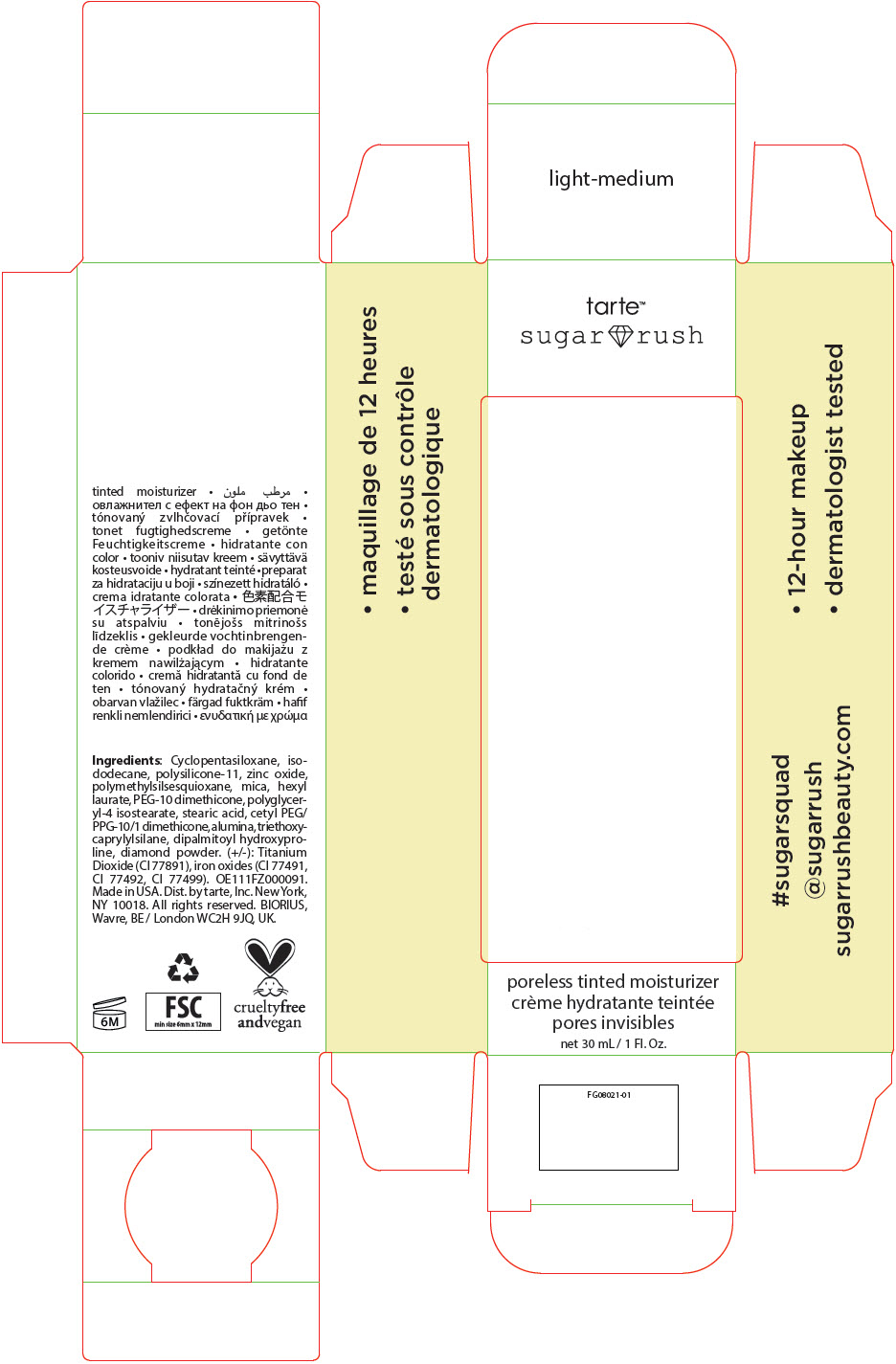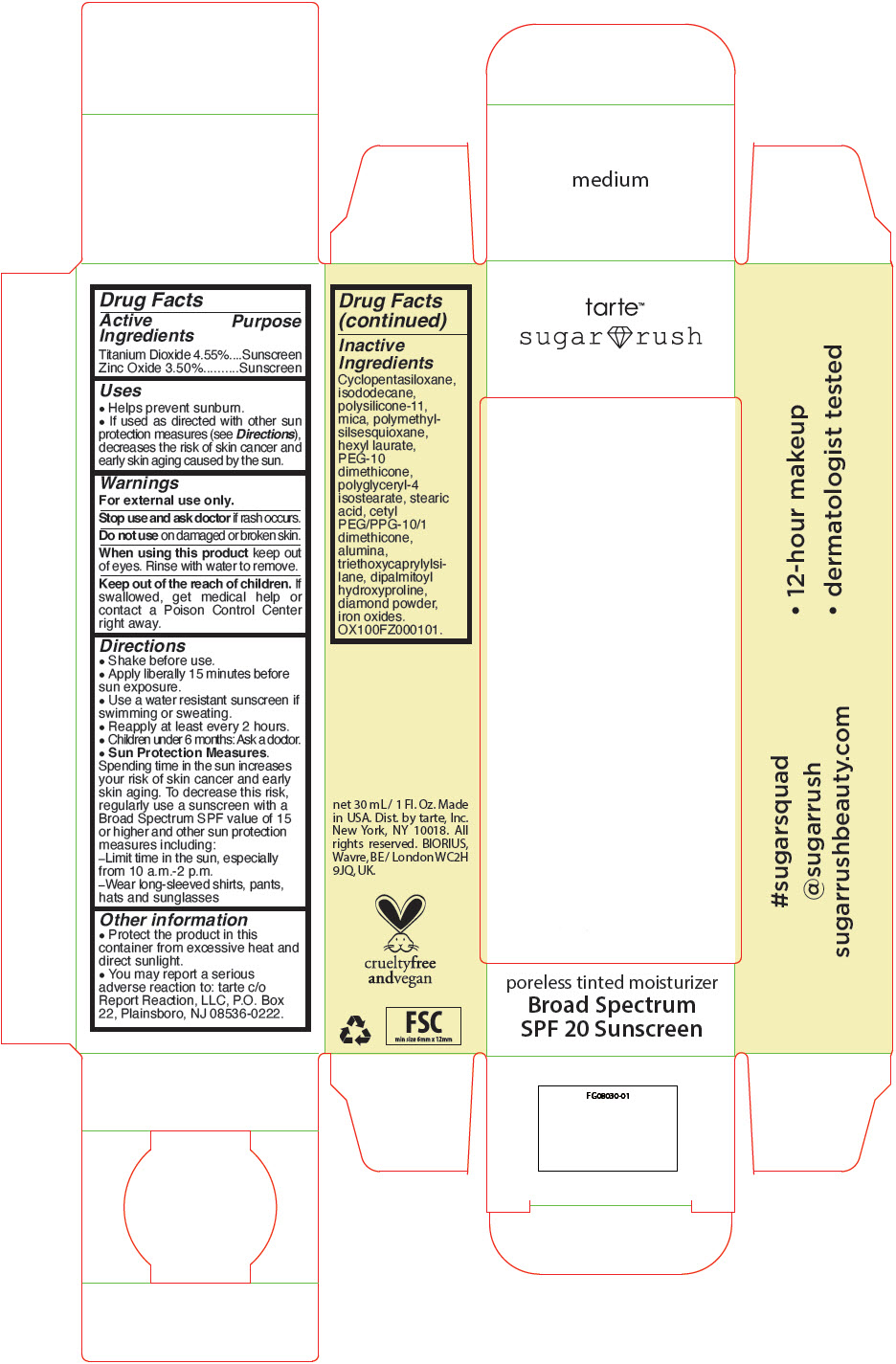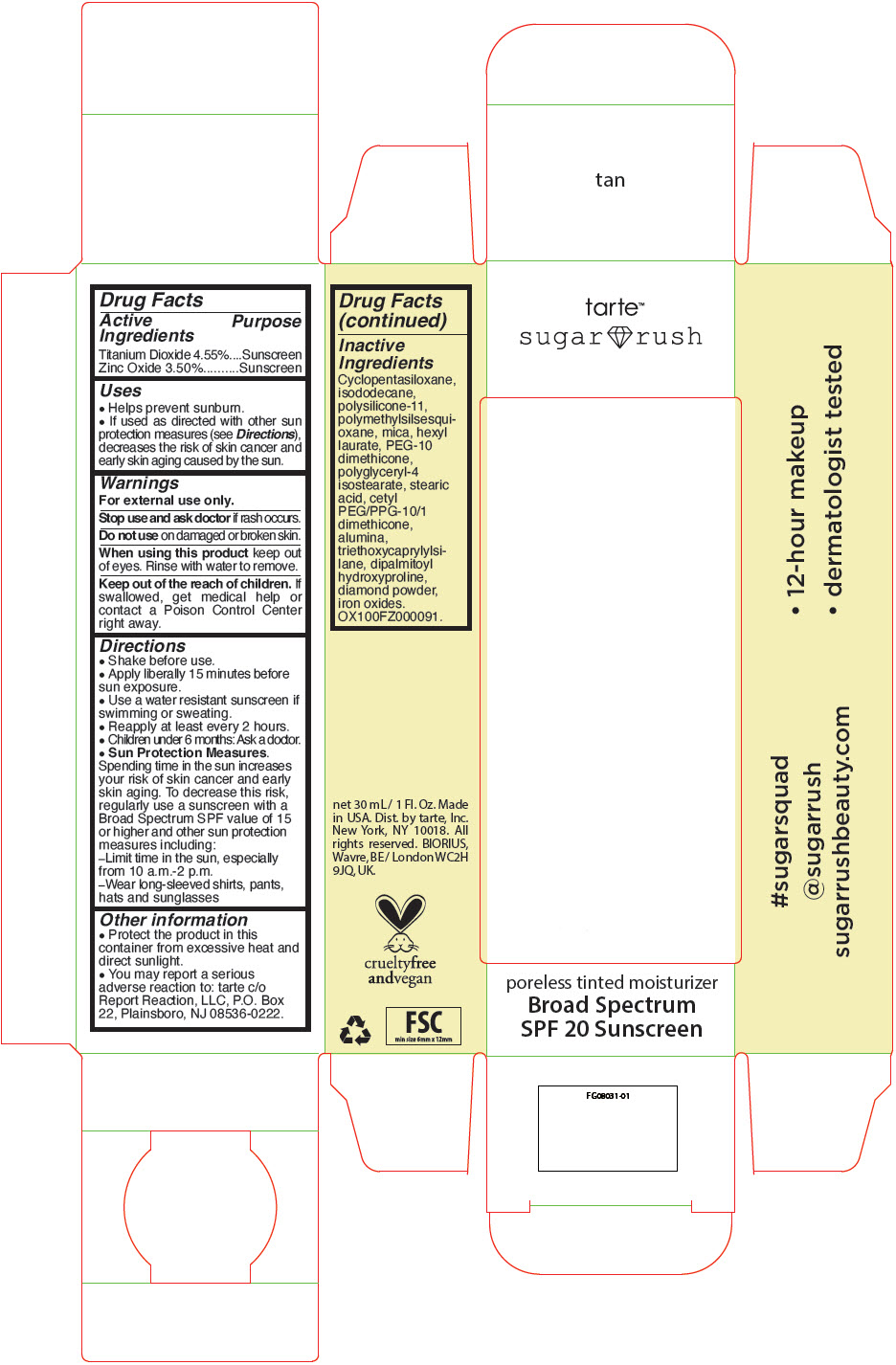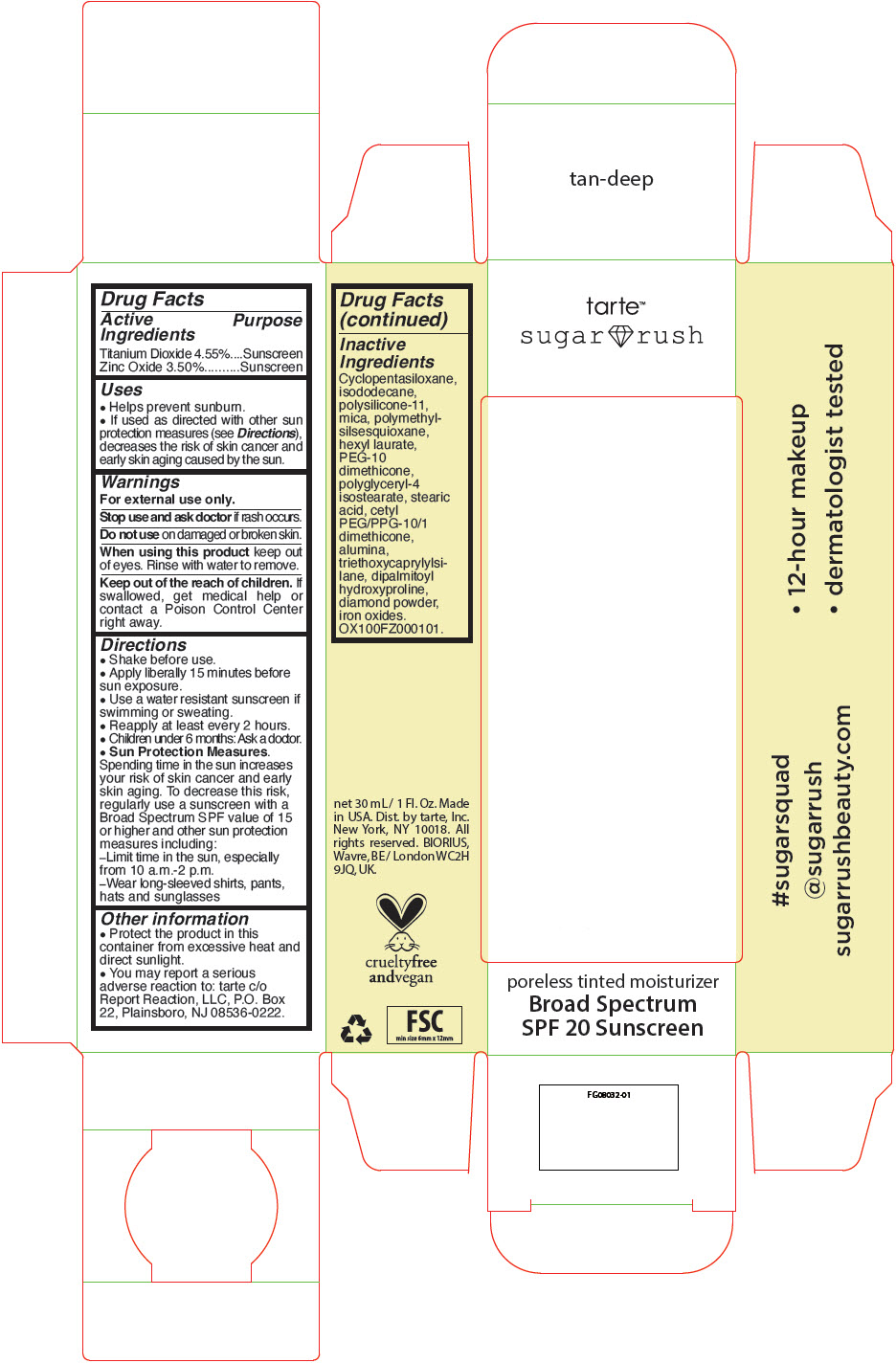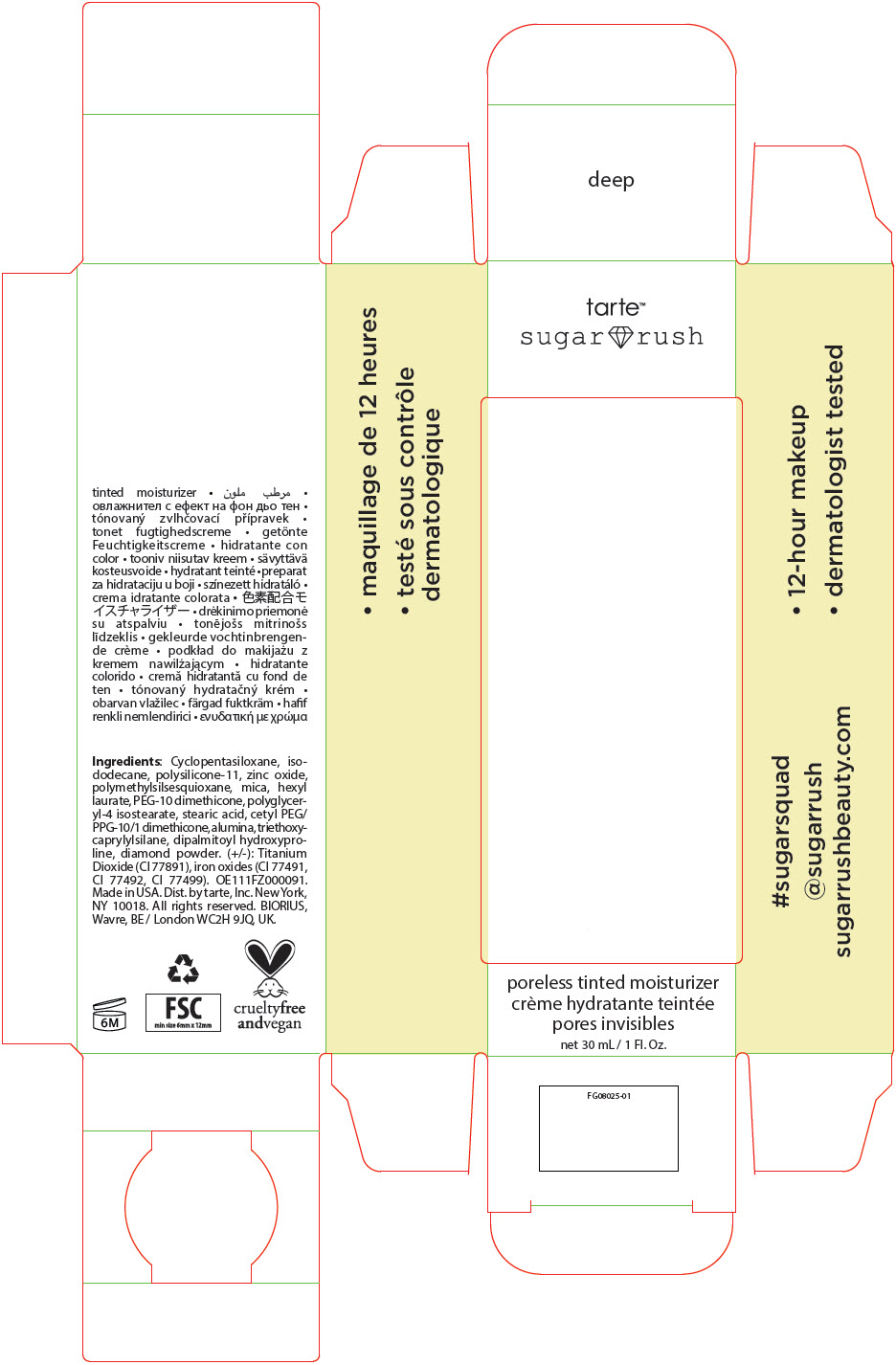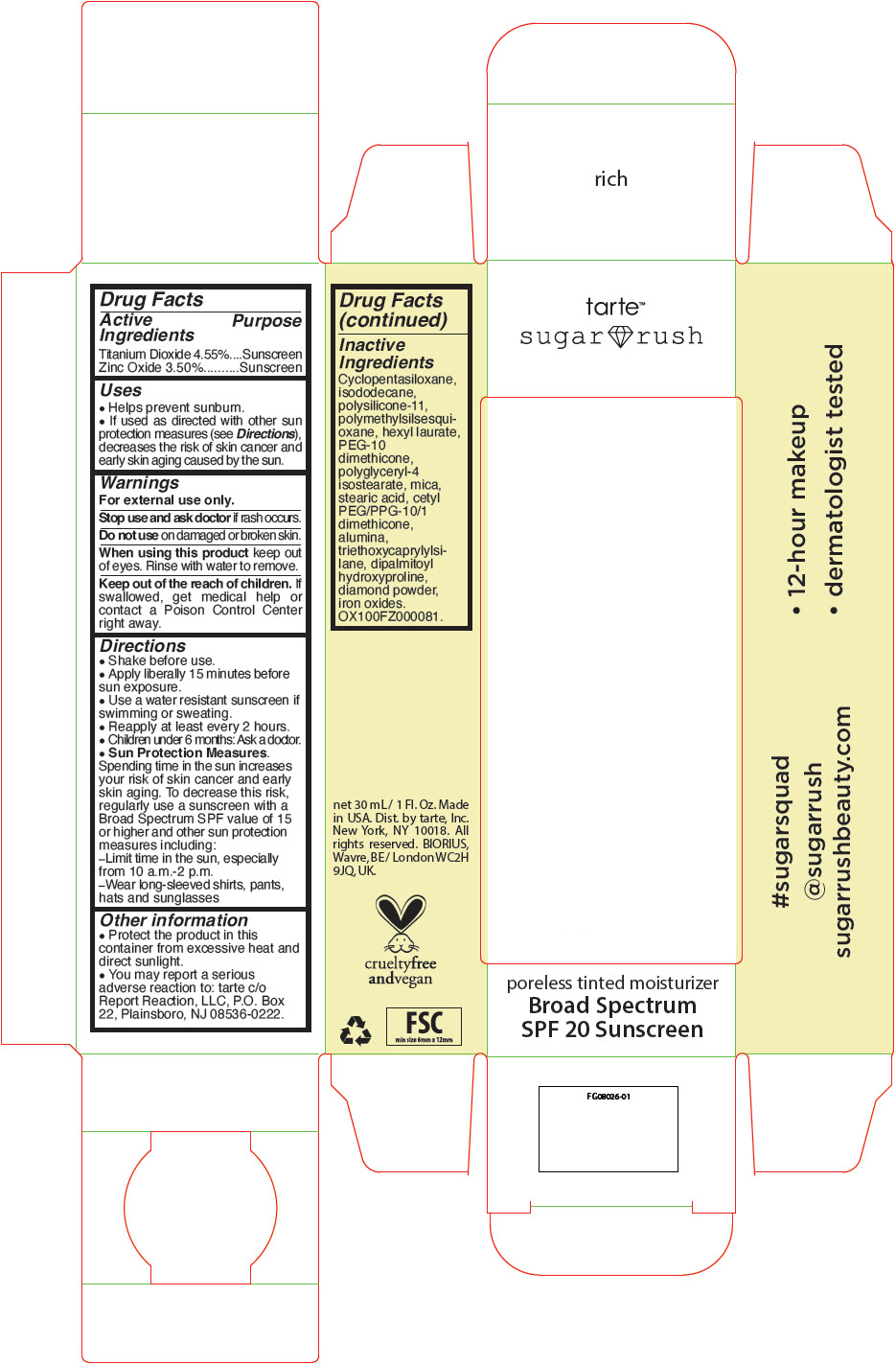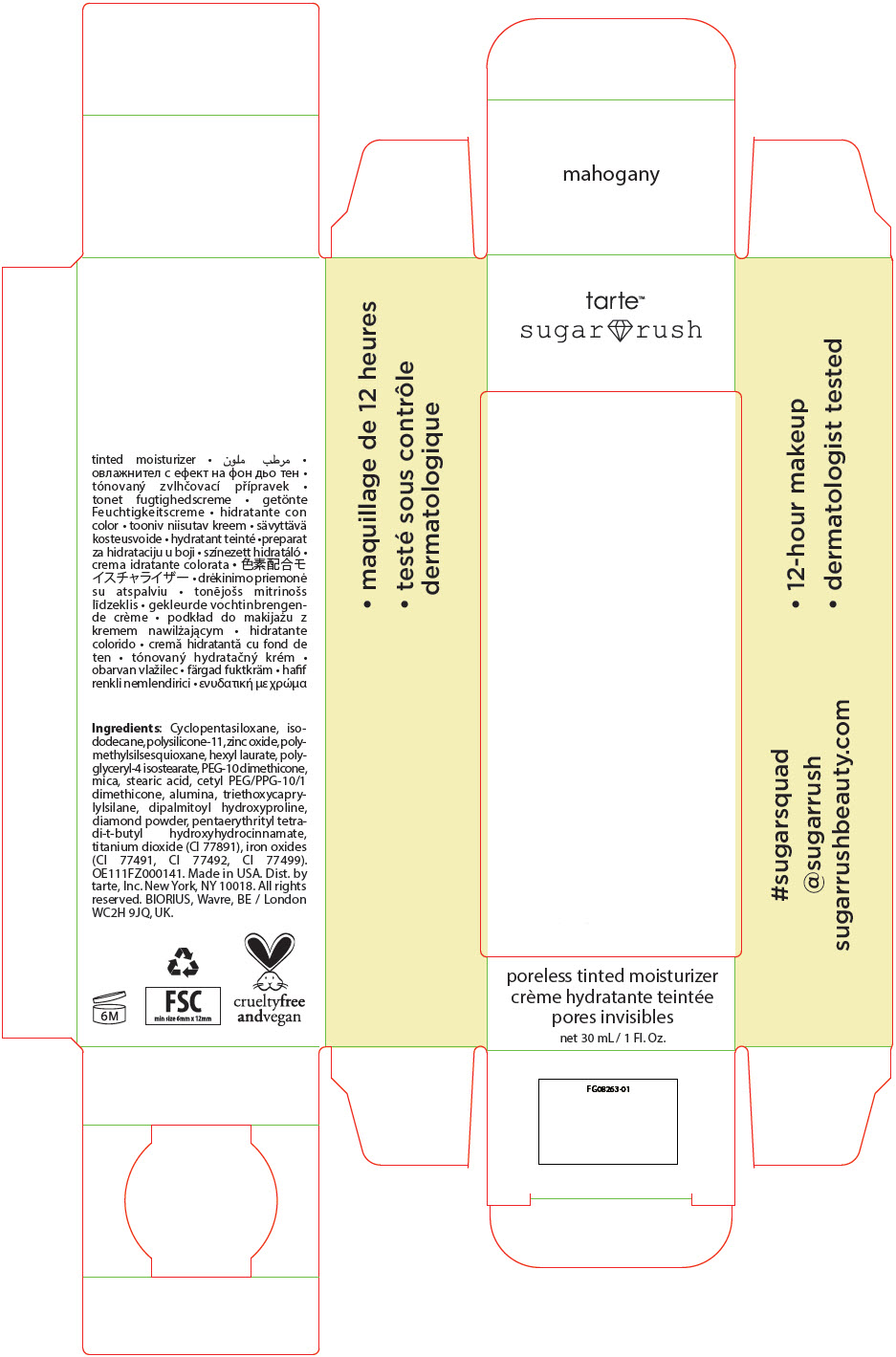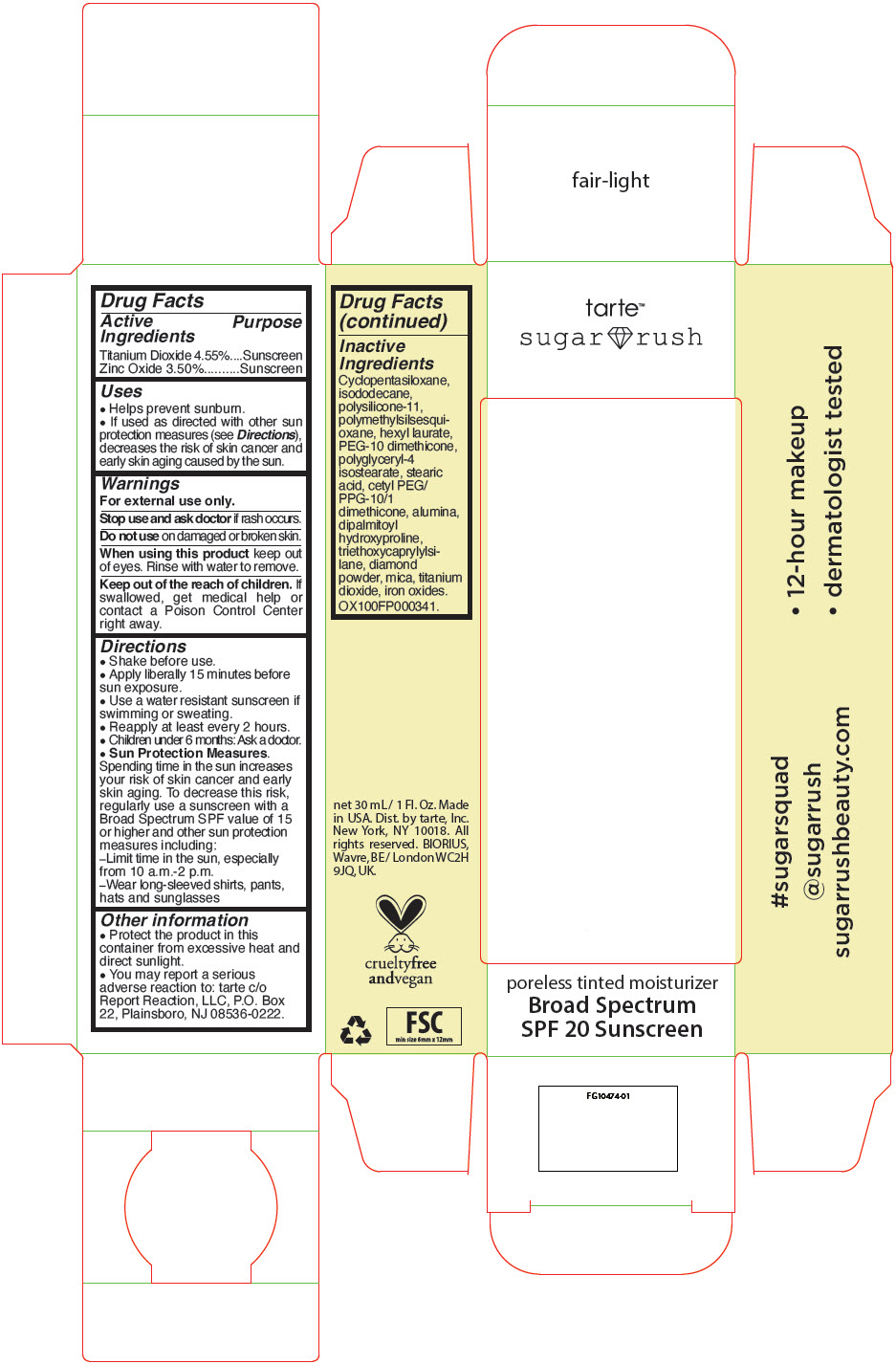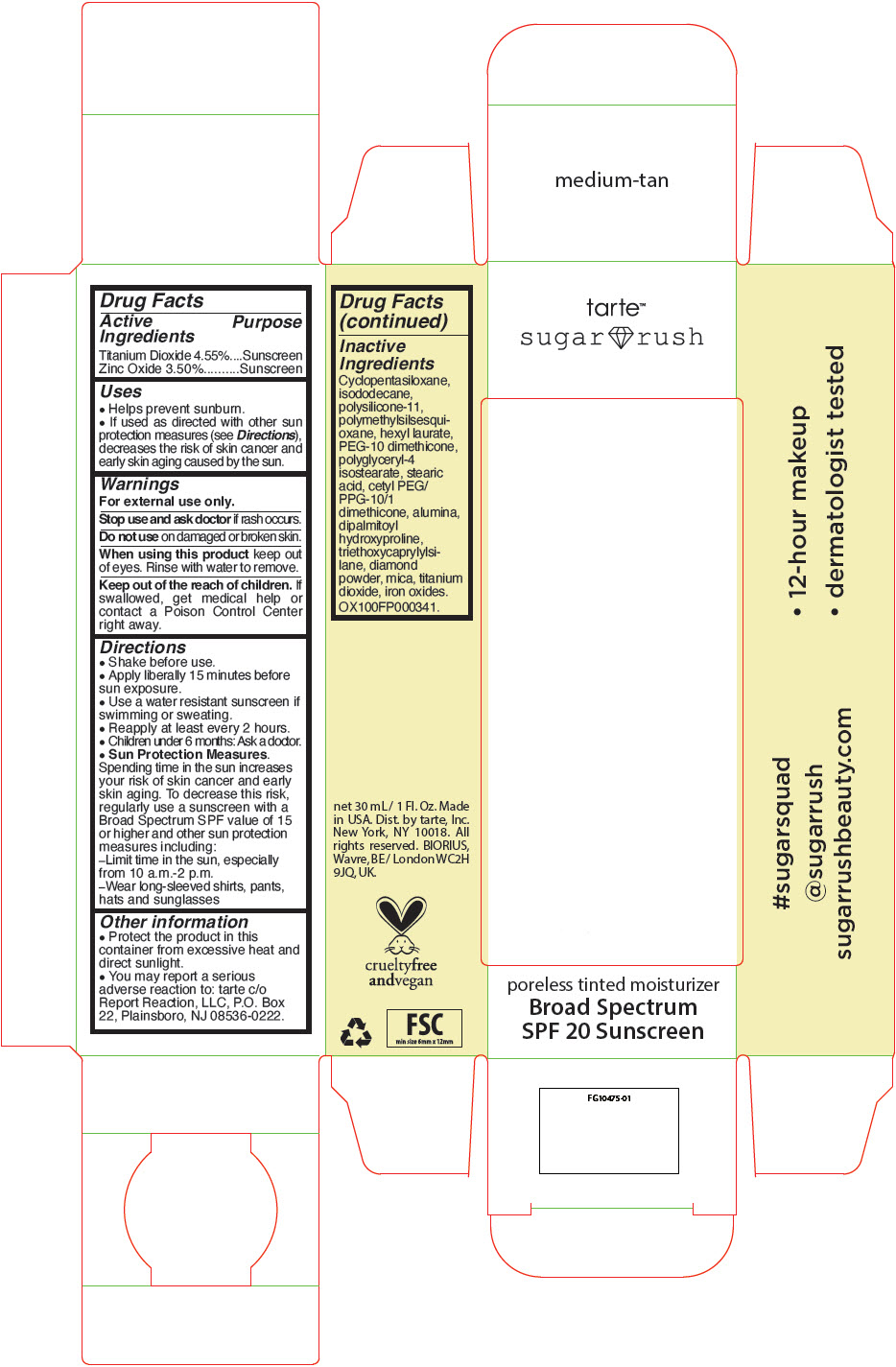 DRUG LABEL: sugar rush skin treat poreless tinted moisturizer Broad Spectrum SPF 20 Sunscreen 
NDC: 51060-311 | Form: LIQUID
Manufacturer: Tarte, Inc.
Category: otc | Type: HUMAN OTC DRUG LABEL
Date: 20231222

ACTIVE INGREDIENTS: TITANIUM DIOXIDE 45.5 mg/1 mL; ZINC OXIDE 35 mg/1 mL
INACTIVE INGREDIENTS: CYCLOMETHICONE 5; ISODODECANE; DIMETHICONE/VINYL DIMETHICONE CROSSPOLYMER (SOFT PARTICLE); POLYMETHYLSILSESQUIOXANE (4.5 MICRONS); HEXYL LAURATE; PEG-10 DIMETHICONE (600 CST); POLYGLYCERYL-4 ISOSTEARATE; CYCLOMETHICONE 6; STEARIC ACID; CETYL PEG/PPG-10/1 DIMETHICONE (HLB 3); ALUMINUM OXIDE; TRIETHOXYCAPRYLYLSILANE; DIPALMITOYL HYDROXYPROLINE; DIAMOND; MICA; FERROSOFERRIC OXIDE; FERRIC OXIDE YELLOW; FERRIC OXIDE RED

sugar rush™ skin treat poreless tinted moisturizer Broad Spectrum SPF 20 Sunscreen

Drug Facts

ACTIVE INGREDIENT

Active Ingredients | Purpose
Titanium Dioxide 4.55% | Sunscreen
Zinc Oxide 3.50% | Sunscreen

Uses

- Helps prevent sunburn.
- If used as directed with other sun protection measures (see Directions), decreases the risk of skin cancer and early skin aging caused by the sun.

Warnings

For external use only.

Stop use and ask doctor if rash occurs.

Do not use on damaged or broken skin.

When using this product keep out of eyes. Rinse with water to remove.

KEEP OUT OF REACH OF CHILDREN

Keep out of the reach of children. If swallowed, get medical help or contact a Poison Control Center right away.

Directions

- Shake before use.
- Apply liberally 15 minutes before sun exposure.
- Use a water resistant sunscreen if swimming or sweating.
- Reapply at least every 2 hours.
- Children under 6 months: Ask a doctor.
- Sun Protection Measures. Spending time in the sun increases your risk of skin cancer and early skin aging. To decrease this risk, regularly use a sunscreen with a Broad Spectrum SPF value of 15 or higher and other sun protection measures including:
  - Limit time in the sun, especially from 10 a.m.-2 p.m.
  - Wear long-sleeved shirts, pants, hats and sunglasses

Other information

- Protect the product in this container from excessive heat and direct sunlight.
- You may report a serious adverse reaction to: tarte c/o Report Reaction, LLC, P.O. Box 22, Plainsboro, NJ 08536-0222.

Inactive Ingredients

Cyclopentasiloxane, isododecane, mica, polysilicone-11, polymethylsilsesquioxane, hexyl laurate, PEG-10 dimethicone, polyglyceryl-4 isostearate, stearic acid, cetyl PEG/PPG-10/1 dimethicone, alumina, dipalmitoyl hydroxyproline, triethoxycaprylylsilane, diamond powder, iron oxides. OX100FZ000071.

Dist. by tarte, Inc. NY 10018.

PRINCIPAL DISPLAY PANEL - 30 mL Tube Carton - Fair

tarte™
sugar rush

poreless tinted moisturizer

net 30 mL / 1 Fl. Oz.

PRINCIPAL DISPLAY PANEL - 30 mL Tube Carton - Light

tarte™
sugar rush

poreless tinted moisturizer

net 30 mL / 1 Fl. Oz.

PRINCIPAL DISPLAY PANEL - 30 mL Tube Carton - Light-Medium

tarte™
sugar rush

poreless tinted moisturizer

net 30 mL / 1 Fl. Oz.

PRINCIPAL DISPLAY PANEL - 30 mL Tube Carton - Medium

tarte™
sugar rush

poreless tinted moisturizer
Broad Spectrum
SPF 20 Sunscreen

PRINCIPAL DISPLAY PANEL - 30 mL Tube Carton - Tan

tarte™
sugar rush

poreless tinted moisturizer
Broad Spectrum
SPF 20 Sunscreen

PRINCIPAL DISPLAY PANEL - 30 mL Tube Carton - Tan-Deep

tarte™
sugar rush

poreless tinted moisturizer
Broad Spectrum
SPF 20 Sunscreen

PRINCIPAL DISPLAY PANEL - 30 mL Tube Carton - Deep

tarte™
sugar rush

poreless tinted moisturizer

net 30 mL / 1 Fl. Oz.

PRINCIPAL DISPLAY PANEL - 30 mL Tube Carton - Rich

tarte™
sugar rush

poreless tinted moisturizer
Broad Spectrum
SPF 20 Sunscreen

PRINCIPAL DISPLAY PANEL - 30 mL Tube Carton - Mahogany

tarte™
sugar rush

poreless tinted moisturizer

net 30 mL / 1 Fl. Oz.

PRINCIPAL DISPLAY PANEL - 30 mL Tube Carton - Fair-Light

tarte™
sugar rush

poreless tinted moisturizer
Broad Spectrum
SPF 20 Sunscreen

PRINCIPAL DISPLAY PANEL - 30 mL Tube Carton - Medium-Tan

tarte™
sugar rush

poreless tinted moisturizer
Broad Spectrum
SPF 20 Sunscreen